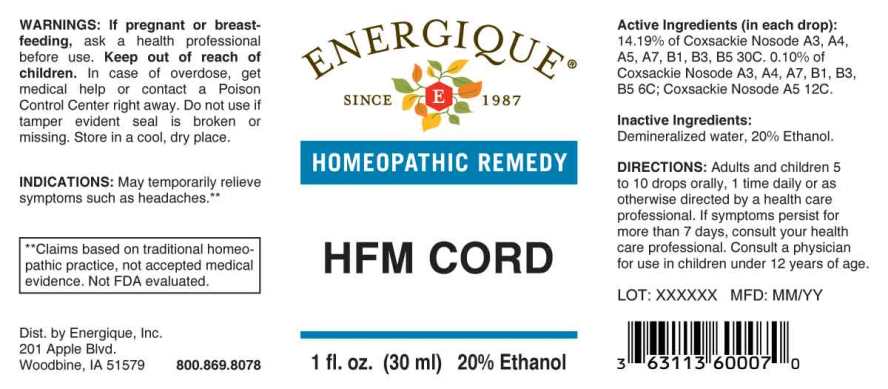 DRUG LABEL: HFM CORD
NDC: 44911-0601 | Form: LIQUID
Manufacturer: Energique, Inc.
Category: homeopathic | Type: HUMAN OTC DRUG LABEL
Date: 20241025

ACTIVE INGREDIENTS: HUMAN COXSACKIEVIRUS A 6 [hp_C]/1 mL; HUMAN COXSACKIEVIRUS A7 6 [hp_C]/1 mL; HUMAN COXSACKIEVIRUS B 6 [hp_C]/1 mL; HUMAN COXSACKIEVIRUS B1 6 [hp_C]/1 mL; HUMAN COXSACKIEVIRUS B3 12 [hp_C]/1 mL
INACTIVE INGREDIENTS: WATER; ALCOHOL

DRUG FACTS:

ACTIVE INGREDIENTS:

(in each drop): 14.19% of Coxsackie Nosode A3, A4, A5, A7, B1, B3, B5, 30C. 0.10% of Coxsackie Nosode A5 12C; Coxsackie Nosode A3, A4, A7, B1, B3, B5, 6C.

INDICATIONS:

May temporarily relieve symptoms such as headaches.**

**Claims based on traditional homeopathic practice, not accepted medical evidence. Not FDA evaluated.

WARNINGS:

If pregnant or breast-feeding, ask a health professional before use.

Keep out of reach of children. In case of overdose, get medical help or contact a Poison Control Center right away.

Do not use if tamper evident seal is broken or missing. Store in a cool, dry place.

Keep out of reach of children. In case of overdose, get medical help or contact a Poison Control Center right away.

DIRECTIONS:

Adults and children 5 to 10 drops orally, 1 time daily or as otherwise directed by a health care professional. If symptoms persist for more than 7 days, consult your health care professional. Consult a physician for use in children under 12 years of age.

INDICATIONS:

May temporarily relieve symptoms such as headaches.**

**Claims based on traditional homeopathic practice, not accepted medical evidence. Not FDA evaluated.

INACTIVE INGREDIENTS:

Demineralized water, 20% Ethanol.

QUESTIONS:

Dist. by Energique, Inc.
201 Apple Blvd
Woodbine, IA 51579 800-869-8078

PACKAGE LABEL DISPLAY:

ENERGIQUE

SINCE 1987

HOMEOPATHIC REMEDY

HFM CORD

1 fl. oz. (30 ml)